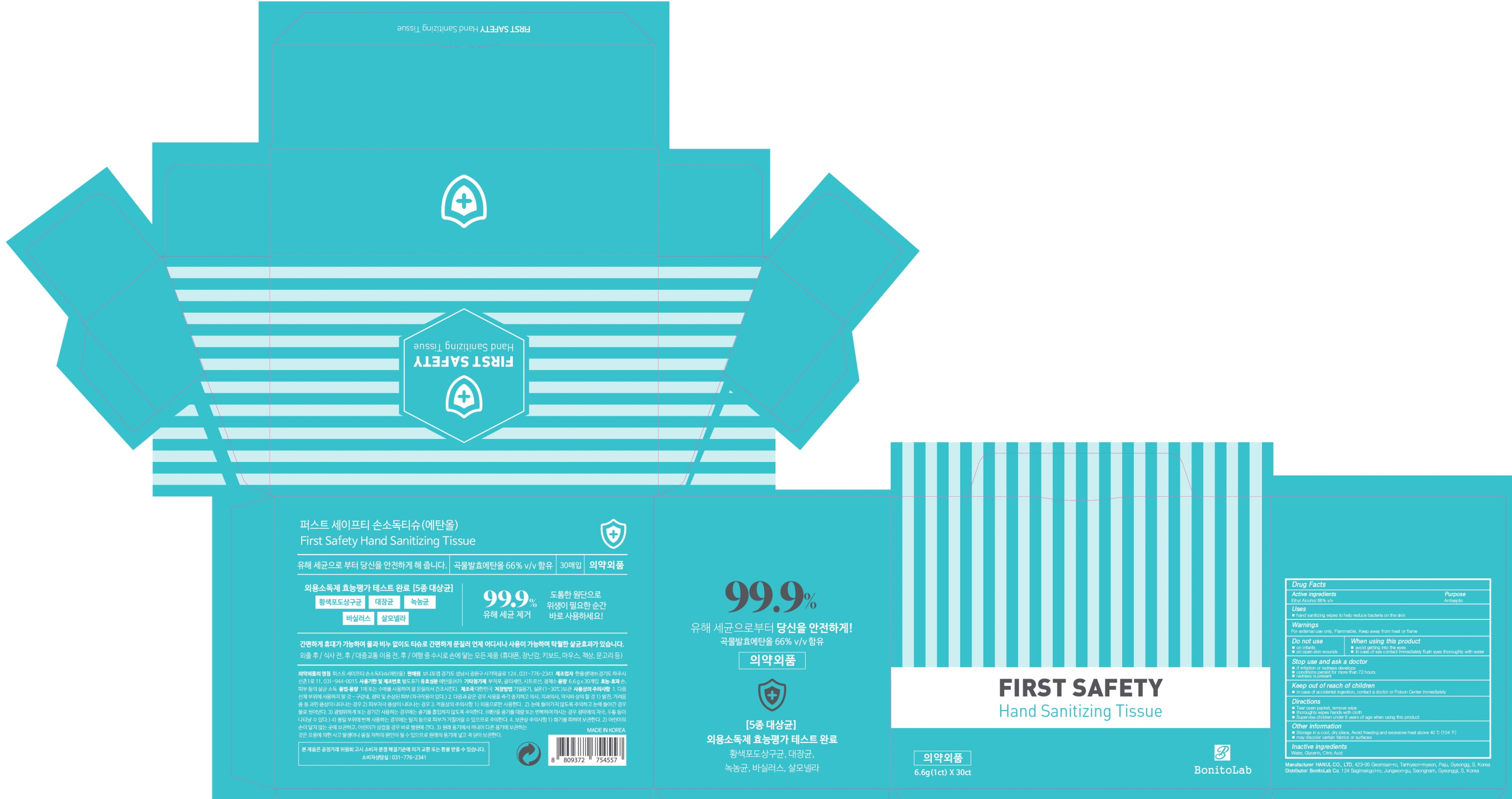 DRUG LABEL: First safety hand sanitizing tissue
NDC: 79984-010 | Form: CLOTH
Manufacturer: BonitoLab Co.
Category: otc | Type: HUMAN OTC DRUG LABEL
Date: 20200804

ACTIVE INGREDIENTS: Alcohol 66 1/100 1
INACTIVE INGREDIENTS: Water; Glycerin; CITRIC ACID MONOHYDRATE

ACTIVE INGREDIENT

Ethy Alcohol 66% v/v

INACTIVE INGREDIENTS

Water, Glycerin, Citric Acid

PURPOSE

Antiseptic

WARNINGS

For external use only. Flammable. Keep away from heat or flame
--------------------------------------------------------------------------------------------------------
Do not use
■ on infants
■ on open skin wounds
--------------------------------------------------------------------------------------------------------
When using this product
■ avoid getting into the eyes
■ In case of eye contact immediately flush eyes thoroughly with water
--------------------------------------------------------------------------------------------------------
Stop use and ask a doctor
■ if irritation or redness develops
■ conditions persist for more than 72 hours
■ redness is present

KEEP OUT OF REACH OF CHILDREN

■ in case of accidental ingestion, contact a doctor or Poison Center immediately

Uses

■ hand sanitizing wipes to help reduce bacteria on the skin

Directions

■ Tear open packet, remove wipe
■ thoroughly wipes hands with cloth
■ Supervise children under 6 years of age when using this product

Other Information

■ Storage in a cool, dry place, Avoid freezing and excessive heat above 40 ℃ (104 ℉)
■ may discolor certain fabrics or surfaces